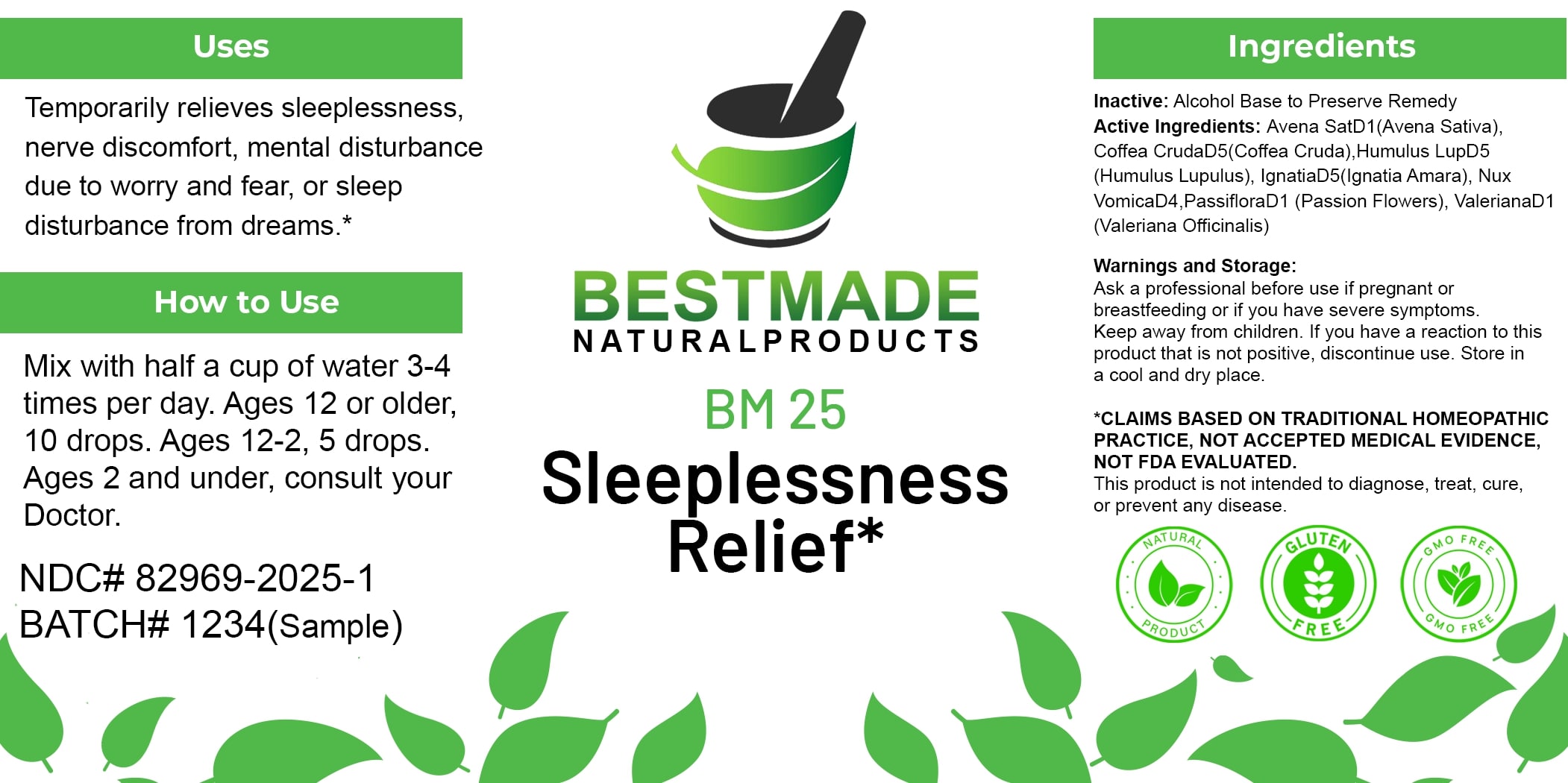 DRUG LABEL: Bestmade Natural Products
NDC: 82969-2025 | Form: LIQUID
Manufacturer: Bestmade Natural Products
Category: homeopathic | Type: HUMAN OTC DRUG LABEL
Date: 20250123

ACTIVE INGREDIENTS: AVENA SATIVA FLOWERING TOP 30 [hp_C]/30 [hp_C]; STRYCHNOS NUX-VOMICA SEED 30 [hp_C]/30 [hp_C]; PASSIFLORA INCARNATA FLOWERING TOP 30 [hp_C]/30 [hp_C]; VALERIAN 30 [hp_C]/30 [hp_C]; ARABICA COFFEE BEAN 30 [hp_C]/30 [hp_C]; HOPS 30 [hp_C]/30 [hp_C]; STRYCHNOS IGNATII SEED 30 [hp_C]/30 [hp_C]
INACTIVE INGREDIENTS: ALCOHOL 30 [hp_C]/30 [hp_C]

BM25

DOSAGE AND ADMINISTRATION

How to Use

Mix with half a cup of water 3-4 times per day. Ages 12 or older, 10 drops. Ages 12-2, 5 drops. Ages 2 and under, consult your Doctor.

INACTIVE INGREDIENT

Ingredients

Inactive: Alcohol Base to Preserve Remedy

Active Ingredients:

Avena SatD1(Avena Sativa), Coffea CrudaD5(Coffea Cruda), Humulus LupD5 (Humulus Lupulus), IgnatiaD5(Ignatia Amara), Nux VomicaD4, PassifloraD1 (Passion Flowers), ValerianaD1 (Valeriana Officinalis)

Uses

Temporarily relieves sleeplessness, nerve discomfort, mental disturbance due to worry and fear, or sleep disturbance from dreams.*

*CLAIMS BASED ON TRADITIONAL HOMEOPATHIC PRACTICE, NOT ACCEPTED MEDICAL EVIDENCE, NOT FDA EVALUATED.

This product is not intended to diagnose, treat, cure, or prevent any disease.

Uses

Temporarily relieves sleeplessness, nerve discomfort, mental disturbance due to worry and fear, or sleep disturbance from dreams.*

*CLAIMS BASED ON TRADITIONAL HOMEOPATHIC PRACTICE, NOT ACCEPTED MEDICAL EVIDENCE, NOT FDA EVALUATED.

This product is not intended to diagnose, treat, cure, or prevent any disease.

KEEP OUT OF REACH OF CHILDREN

Warnings and Storage:

Ask a professional before use if pregnant or breastfeeding or if you have severe symptoms. Keep away from children. If you have a reaction to this product that is not positive, discontinue use. Store in a cool and dry place.

Warnings and Storage:

Ask a professional before use if pregnant or breastfeeding or if you have severe symptoms. Keep away from children. If you have a reaction to this product that is not positive, discontinue use. Store in a cool and dry place.

*CLAIMS BASED ON TRADITIONAL HOMEOPATHIC PRACTICE, NOT ACCEPTED MEDICAL EVIDENCE, NOT FDA EVALUATED.

This product is not intended to diagnose, treat, cure, or prevent any disease.

Entire package label